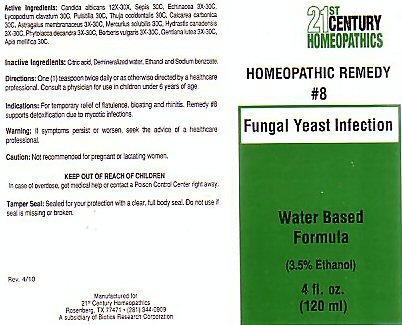 DRUG LABEL: CENTURY 21 FUNGAL YEAST INFECTION
NDC: 63972-008 | Form: LIQUID
Manufacturer: 21st Century Homeopathics, Inc
Category: homeopathic | Type: HUMAN OTC DRUG LABEL
Date: 20100101

ACTIVE INGREDIENTS: CANDIDA ALBICANS 30 [hp_X]/5 mL; SEPIA OFFICINALIS JUICE 30 [hp_C]/5 mL; ECHINACEA, UNSPECIFIED 30 [hp_C]/5 mL; LYCOPODIUM CLAVATUM SPORE 30 [hp_C]/5 mL; PULSATILLA VULGARIS 30 [hp_C]/5 mL; THUJA OCCIDENTALIS LEAFY TWIG 30 [hp_C]/5 mL; OYSTER SHELL CALCIUM CARBONATE, CRUDE 30 [hp_C]/5 mL; ASTRAGALUS PROPINQUUS ROOT 30 [hp_C]/5 mL; MERCURIUS SOLUBILIS 30 [hp_C]/5 mL; GOLDENSEAL 30 [hp_C]/5 mL; PHYTOLACCA AMERICANA ROOT 30 [hp_C]/5 mL; BERBERIS VULGARIS ROOT BARK 30 [hp_C]/5 mL; GENTIANA LUTEA ROOT 30 [hp_C]/5 mL; APIS MELLIFERA 30 [hp_C]/5 mL
INACTIVE INGREDIENTS: CITRIC ACID MONOHYDRATE; WATER; ALCOHOL; SODIUM BENZOATE

Active Ingredients

Active Ingredients: Candida albicans 12X-30X, Sepia 30C, Echinacea 3X-30C, Lycopodium clavatum 30C, Pulsuitilla 30C, Thuja occidentalis 30C, Calcarea carbonica 30C, Astragalus membranaceus 3X-30C. Mercurius solubilis 30C, Hydrastis canadensis 3X-30C, Phytolacca decandra 3X-30C, Berberis vulgaris 3X-30C, Gentiana lutea 3x-30C, Apis mellifica 30C

Inactive Ingredients

Inactive Ingredients: Citric acid, demineralized water, Ethanol and Sodium benzoate.

Directions For Use

Directions: One (1) teaspoon twice daily or as directed by a healthcare professional.

Indications

Indications: For temporary relief of flatulence, bloating and rhinitis. Remedy #8 supports detoxification due to mycotic infections.

Keep Out Of Reach Of Children

In case of overdose, get medical help or contact a Poison Control Center right away.

Purpose

Fungal Yeast Infection

Warnings

Warning: If symptoms persist or worsen, seek the advice of a healthcare profeccional.
Caution: Not recommended for pregnant or lactating women.

Product Label

21st CENTURY HOMEOPATHICS
HOMEOPATHIC REMEDY #8 Fungal Yeast Infection
Water based Formula (3.5% Ethanol) 4 fl. oz. (120ml)
Tamper Seal: Sealed for your protection with a clear, full body seal. Do not use if seal is missing or broken.
Rev 4/10 Manufactured for 21st Century Homeopathics Rosenburg, Tx 77471 (281) 344-0909 A subsidiary of Biotics Research Corporation